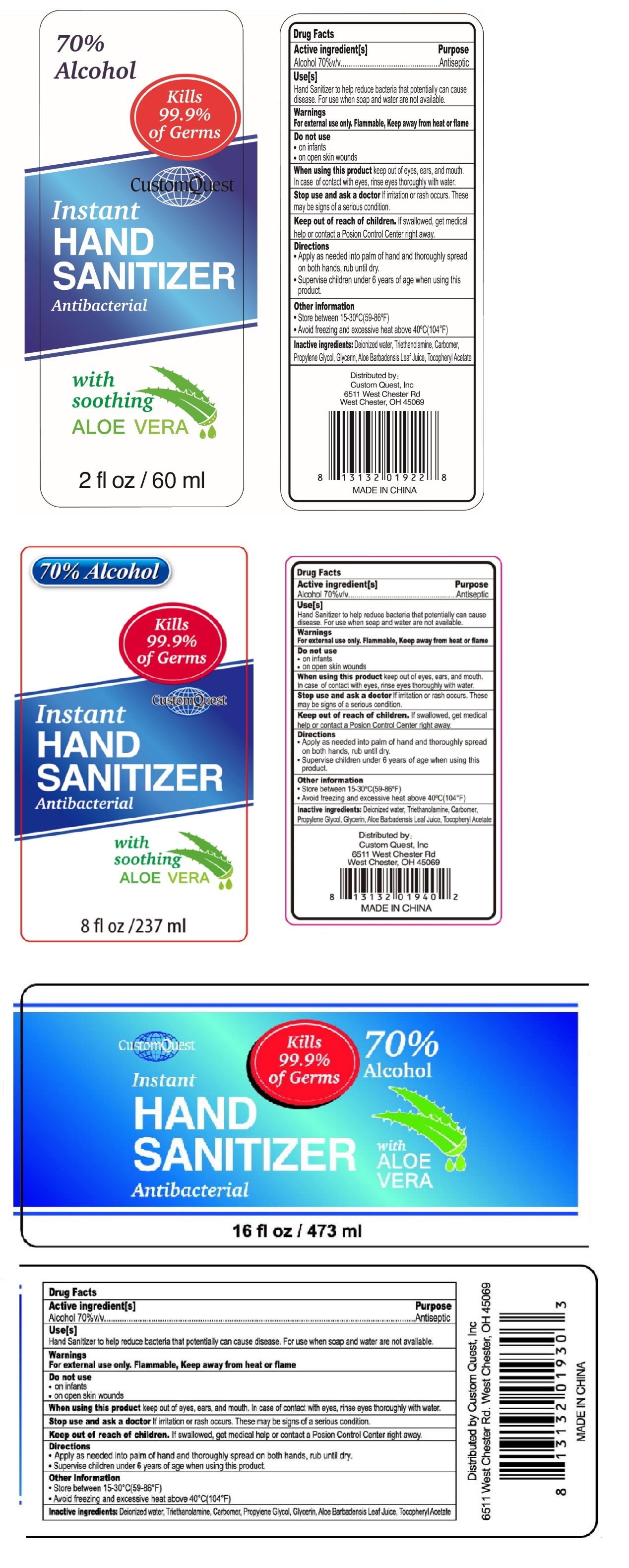 DRUG LABEL: Custom Quest Hand Sanitizer
NDC: 74876-655 | Form: LIQUID
Manufacturer: Custom Quest, Inc.
Category: otc | Type: HUMAN OTC DRUG LABEL
Date: 20200527

ACTIVE INGREDIENTS: ALCOHOL 70 mL/100 mL
INACTIVE INGREDIENTS: WATER; TROLAMINE; CARBOMER HOMOPOLYMER, UNSPECIFIED TYPE; PROPYLENE GLYCOL; GLYCERIN; ALOE VERA LEAF; .ALPHA.-TOCOPHEROL ACETATE

CustomQuest Instant HAND SANITIZER

Active ingredient[s]

Alcohol 70%v/v

Purpose

Antiseptic

Use[s]

Hand Sanitizer to help reduce bacteria that potentially can cause disease. For use when soap and water are not available.

Warnings

For external use only. Flammable, Keep away from heat or flame

Do not use

- on infants
- on open skin wounds

When using this product keep out of eyes, ears, and mouth. In case of contact with eyes, rinse eyes thoroughly with water.

Stop use and ask a doctor If irritation or rash occurs. These may be signs of a serious condition.

Keep out of reach of children. If swallowed, get medical help or contact a Poison Control Center right away.

Directions

- Apply as needed into palm of hand and thoroughly spread on both hands, rub until dry.
- Supervise children under 6 years of age when using this product.

Other information

- Store between 15-30°C(59-86°F).
- Avoid freezing and excessive heat above 40°C(104°F)

INACTIVE INGREDIENT

Inactive ingredients: Deionized water, Triethanolamine, Carbomer, Propylene Glycol, Glycerin, Aloe Barbadensis Leaf Juice, Tocopheryl Acetate

Kills 99.9% of Germs

Antibacterial

with soothing ALOE VERA

Distributed by Custom Quest, Inc

6511 West Chester Rd. West Chester, OH 45069

MADE IN CHINA